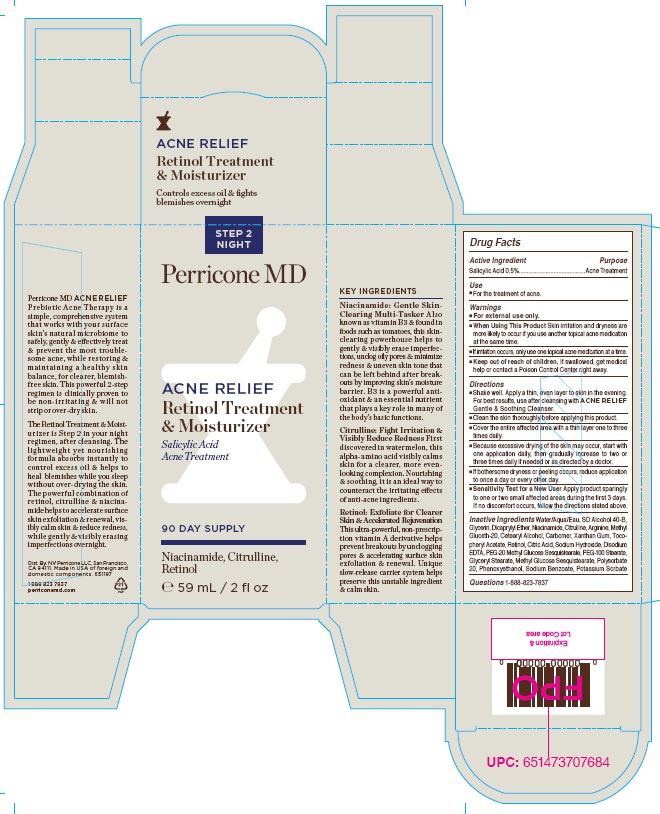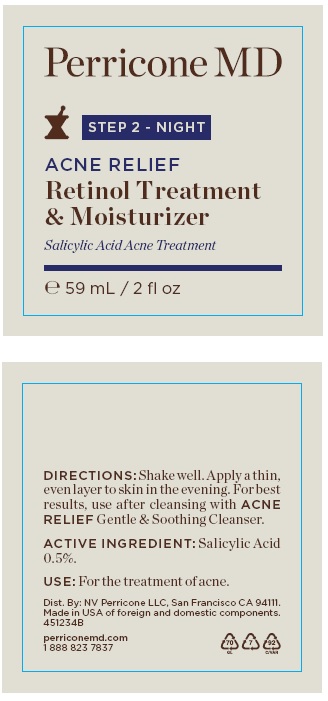 DRUG LABEL: Acne Relief Retinol Treatment and Moisturizer
NDC: 45634-101 | Form: LOTION
Manufacturer: NV Perricone LLC
Category: otc | Type: HUMAN OTC DRUG LABEL
Date: 20220210

ACTIVE INGREDIENTS: SALICYLIC ACID 0.295 g/59 mL
INACTIVE INGREDIENTS: WATER; ALCOHOL; GLYCERIN; DICAPRYLYL ETHER; NIACINAMIDE; CITRULLINE; ARGININE; METHYL GLUCETH-20; CETOSTEARYL ALCOHOL; CARBOXYPOLYMETHYLENE; PHENOXYETHANOL; CITRIC ACID MONOHYDRATE; PEG-20 METHYL GLUCOSE SESQUISTEARATE; PEG-100 STEARATE; GLYCERYL MONOSTEARATE; METHYL GLUCOSE SESQUISTEARATE; XANTHAN GUM; SODIUM HYDROXIDE; .ALPHA.-TOCOPHEROL ACETATE; SODIUM BENZOATE; RETINOL; POLYSORBATE 20; EDETATE DISODIUM ANHYDROUS

ACNE RELIEF RETINOL TREATMENT & MOISTURIZER STEP 2 - NIGHT

Drug Facts

Active Ingredient
Salicylic Acid 0.5%

Purpose
Acne Treatment

Use
■ For the treatment of acne.

Warnings
■ For external use only.
■ When Using This Product Skin irritation and dryness are
more likely to occur if you use another topical acne medication
at the same time.
■ If irritation occurs, only use one topical acne medication at a time.
■ Keep out of reach of children. If swallowed, get medical
help or contact a Poison Control Center right away.

Directions
■ Shake well. Apply a thin, even layer to skin in the evening.
For best results, use after cleansing with ACNE RELIEF
Gentle & Soothing Cleanser.
■ Clean the skin thoroughly before applying this product.
■ Cover the entire affected area with a thin layer one to three
times daily.
■ Because excessive drying of the skin may occur, start with
one application daily, then gradually increase to two or
three times daily if needed or as directed by a doctor.
■ If bothersome dryness or peeling occurs, reduce application
to once a day or every other day.
■ Sensitivity Test for a New User Apply product sparingly
to one or two small affected areas during the first 3 days.
If no discomfort occurs, follow the directions stated above.

INACTIVE INGREDIENT

Inactive Ingredients Water/Aqua/Eau, SD Alcohol 40-B,
Glycerin, Dicaprylyl Ether, Niacinamide, Citrulline, Arginine, Methyl
Gluceth-20, Cetearyl Alcohol, Carbomer, Xanthan Gum, Tocopheryl
Acetate, Retinol, Citric Acid, Sodium Hydroxide, Disodium
EDTA, PEG-20 Methyl Glucose Sesquistearate, PEG-100 Stearate,
Glyceryl Stearate, Methyl Glucose Sesquistearate, Polysorbate
20, Phenoxyethanol, Sodium Benzoate, Potassium Sorbate

Questions 1-888-823-7837

Product Package

ACNE RELIEF

Retinol Treatment
& Moisturizer

Controls excess oil & fights
blemishes overnight

STEP 2
NIGHT

Perricone MD

ACNE RELIEF
Retinol Treatment
& Moisturizer

Salicylic Acid
Acne Treatment

90 DAY SUPPLY

Niacinamide, Citrulline,
Retinol

℮ 59 mL / 2 fl oz

KEY INGREDIENTS
Niacinamide: Gentle Skin-
Clearing Multi-Tasker Also
known as vitamin B3 & found in
foods such as tomatoes, this skin-
clearing powerhouse helps to
gently & visibly erase imperfections,
unclog oily pores & minimize
redness & uneven skin tone that
can be left behind after breakouts
by improving skin’s moisture
barrier. B3 is a powerful antioxidant
& an essential nutrient
that plays a key role in many of
the body’s basic functions.

Citrulline: Fight Irritation &
Visibly Reduce Redness First
discovered in watermelon, this
alpha-amino acid visibly calms
skin for a clearer, more even-
looking complexion. Nourishing
& soothing, it is an ideal way to
counteract the irritating effects
of anti-acne ingredients.

Retinol: Exfoliate for Clearer
Skin & Accelerated Rejuvenation
This ultra-powerful, non-prescription
vitamin A derivative helps
prevent breakouts by unclogging
pores & accelerating surface skin
exfoliation & renewal. Unique
slow-release carrier system helps
preserve this unstable ingredient
& calm skin.

Expiration &
Lot Code area

Perricone MD ACNE RELIEF
Prebiotic Acne Therapy is a
simple, comprehensive system
that works with your surface
skin’s natural microbiome to
safely, gently & effectively treat
& prevent the most troublesome
acne, while restoring &
maintaining a healthy skin
balance, for clearer, blemish-
free skin. This powerful 2-step
regimen is clinically proven to
be non-irritating & will not
strip or over-dry skin.

The Retinol Treatment & Moisturizer
is Step 2 in your night
regimen, after cleansing. The
lightweight yet nourishing
formula absorbs instantly to
control excess oil & helps to
heal blemishes while you sleep
without over-drying the skin.
The powerful combination of
retinol, citrulline & niacinamide
helps to accelerate surface
skin exfoliation & renewal, visibly
calm skin & reduce redness,
while gently & visibly erasing
imperfections overnight.

Dist. By: NV Perricone LLC, San Francisco,
CA 94111. Made in USA of foreign and
domestic components. 651197

1 888 823 7837
perriconemd.com

Outer Box

Bottle

rege